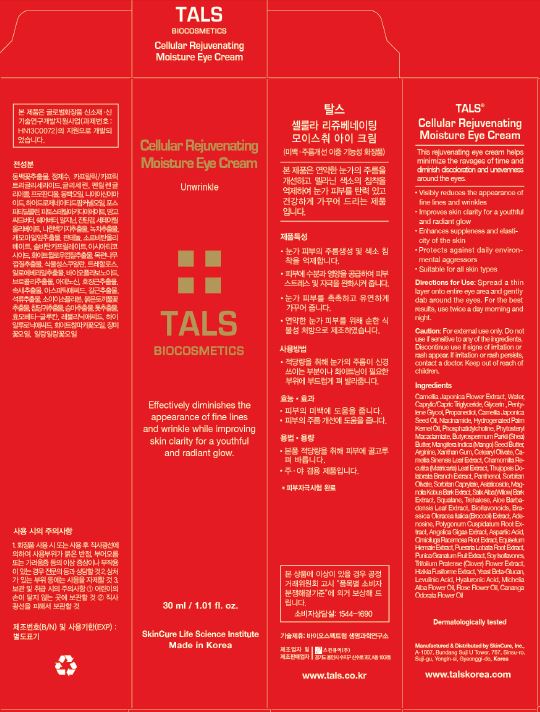 DRUG LABEL: TALS Cellular Rejuvenating Moisture Eye
NDC: 72289-0007 | Form: CREAM
Manufacturer: SKINCURE INC
Category: otc | Type: HUMAN OTC DRUG LABEL
Date: 20190224

ACTIVE INGREDIENTS: GLYCERIN 3 g/100 mL
INACTIVE INGREDIENTS: PANTHENOL; NIACINAMIDE; WATER

Drug Facts

ACTIVE INGREDIENT

glycerin

INACTIVE INGREDIENT

Camellia Japonica Flower Extract
Water(Aqua)
Caprylic/Capric Triglyceride
Glycerin
Pentylene Glycol
Propanediol
Camellia Japonica Seed Oil
Niacinamide
Hydrogenated Palm Kernel Oil
Phosphatidylcholine
Phytosteryl Macadamiate
Butyrospermum Parkii (Shea) Butter
Mangifera Indica (Mango) Seed Butter
Arginine
Xanthan Gum
Cetearyl Olivate
Camellia Sinensis Leaf Extract
Chamomilla Recutita (Matricaria) Leaf Extract
Thujopsis Dolabrata Branch Extract
Panthenol
Sorbitan Olivate
Sorbitan Caprylate
Asiaticoside
Magnolia Kobus Bark Extract
Salix Alba (Willow) Bark Extract
Squalane
Trehalose
Adenosine
Polygonum Cuspidatum Root Extract
Aloe Barbadensis Leaf Extract
Angelica Gigas Extract
Aspartic Acid
Cimicifuga Racemosa Root Extract
Equisetum Hiemale Extract
Pueraria Lobata Root Extract
Punica Granatum Fruit Extract
Soy Isoflavones
Trifolium Pratense (Clover) Flower Extract
Hizikia Fusiforme Extract
Yeast Beta-Glucan
Levulinic Acid
Bioflavonoids
Hyaluronic Acid
Brassica Oleracea Italica (Broccoli) Extract
Michelia Alba Flower Oil
Rose Flower Oil
Cananga Odorata Flower Oil

PURPOSE

this rejuvenating eye cream helps minimize the ravages of time and diminish discoloration and unevenness around the eyes

visibly reduces the appreaance of fine lines and wrinkles

keep out of reach of the children

INDICATIONS AND USAGE

Spread a thin layer onto entire eye area and gently dab around the eyes. For the best results, use twice a day morning and night.

WARNINGS

for external use only

do not use if sensitive to any of the ingredients

discontinue use if signs of irritation or rash appear

if irritation or rash persists, contact a doctor

DOSAGE AND ADMINISTRATION

for external use only